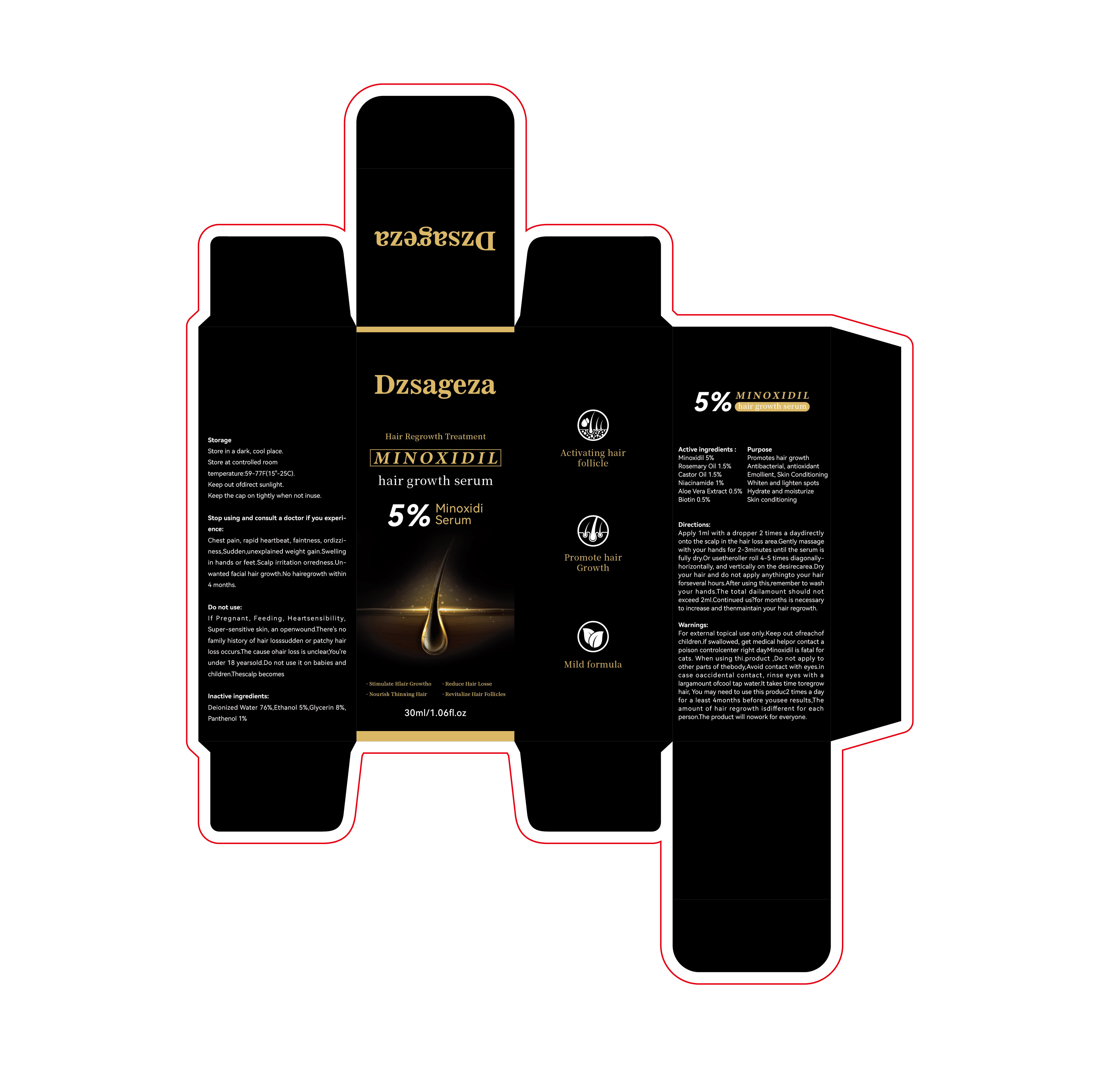 DRUG LABEL: Minodil hair growth solution
NDC: 84279-002 | Form: LIQUID
Manufacturer: Guangzhou Dizhou Biotechnology Co., Ltd
Category: otc | Type: HUMAN OTC DRUG LABEL
Date: 20240427

ACTIVE INGREDIENTS: ALOE VERA LEAF 0.5 g/100 mL; BIOTIN 0.5 g/100 mL; NIACINAMIDE 1 g/100 mL; ROSEMARY OIL 1.5 g/100 mL; MINOXIDIL 5 g/100 mL; CASTOR OIL 1.5 g/100 mL
INACTIVE INGREDIENTS: WATER; GLYCERIN; PANTHENOL; ALCOHOL

84279-002

ACTIVE INGREDIENT

Minoxidil 5%

Rosemary Oil 1.5%

Castor Oil 1.5%

Niacinamide 1%

Aloe Vera Extract 0.5%

Biotin 0.5%

PURPOSE

Promotes hair growth

Antibacterial, antioxidant

Emollient, Skin Conditioning

Whiten and lighten spots

Hydrate and moisturize

Skin conditioning

INDICATIONS AND USAGE

N/A

WARNINGS

For external topical use only.Keep out ofreachof children.if swallowed, get medical helpor contact a poison controlcenter right dayMinoxidil is fatal for cats. When using thi.product ,Do not apply to other parts of thebody,Avoid contact with eyes.in case oaccidental contact, rinse eyes with a largamount ofcool tap water.It takes time toregrow hair, You may need to use this produc2 times a day for a least 4months before yousee results,The amount of hair regrowth isdifferent for each person.The product will nowork for everyone.

DO NOT USE

If Pregnant, Feeding, Heartsensibility, Super-sensitive skin, an openwound.There's no family history of hair losssudden or patchy hair loss occurs.The cause ohair loss is unclear,You're under 18 yearsold.Do not use it on babies and children.Thescalp becomes

WHEN USING

Keep out ofdirect sunlight. Keep the cap on tightly when not inuse.

STOP USE

Stop using and consult a doctor if you experience:Chest pain, rapid heartbeat, faintness, ordizziness,Sudden,unexplained weight gain.Swelling in hands or feet.Scalp irritation orredness.Unwanted facial hair growth.No hairegrowth within 4 months.

KEEP OUT OF REACH OF CHILDREN

You're under 18 yearsold.Do not use it on babies and children.Thescalp becomes

DOSAGE AND ADMINISTRATION

Directions:Apply 1ml with a dropper 2 times a daydirectly onto the scalp in the hair loss area.Gently massage with your hands for 2-3minutes until the serum is fully dry.Or usetheroller roll 4-5 times diagonallyhorizontally, and vertically on the desirecarea.Dry your hair and do not apply anythingto your hair forseveral hours.After using this,remember to wash your hands.The total dailamount should not exceed 2ml.Continued us?for months is necessary to increase and thenmaintain your hair regrowth.

STORAGE AND HANDLING

Store in a dark, cool place.

Store at controlled room temperature:59-77F(15°-25C).

Keep out ofdirect sunlight.

Keep the cap on tightly when not inuse.

INACTIVE INGREDIENT

Deionized Water 76%,Ethanol 5%,Glycerin 8%, Panthenol 1%